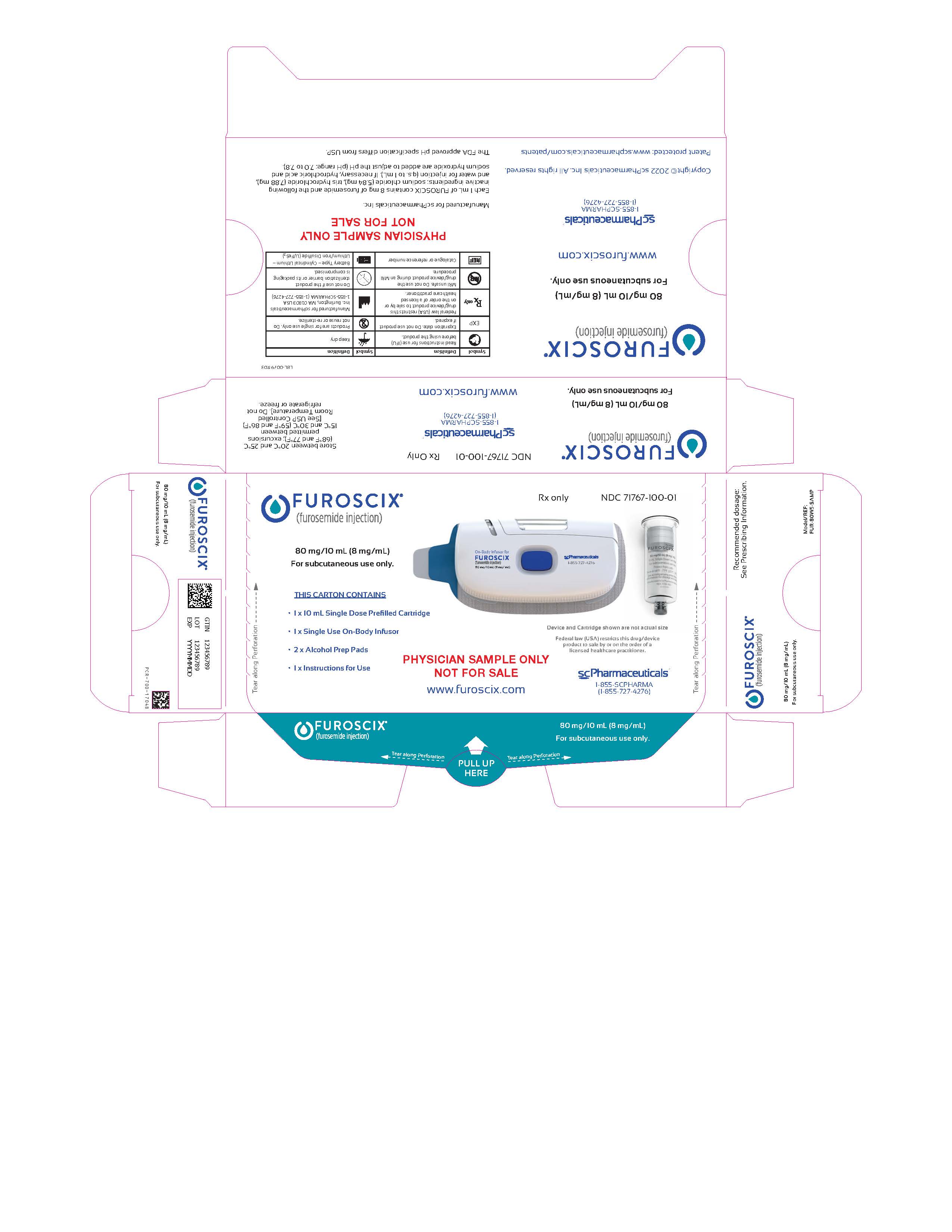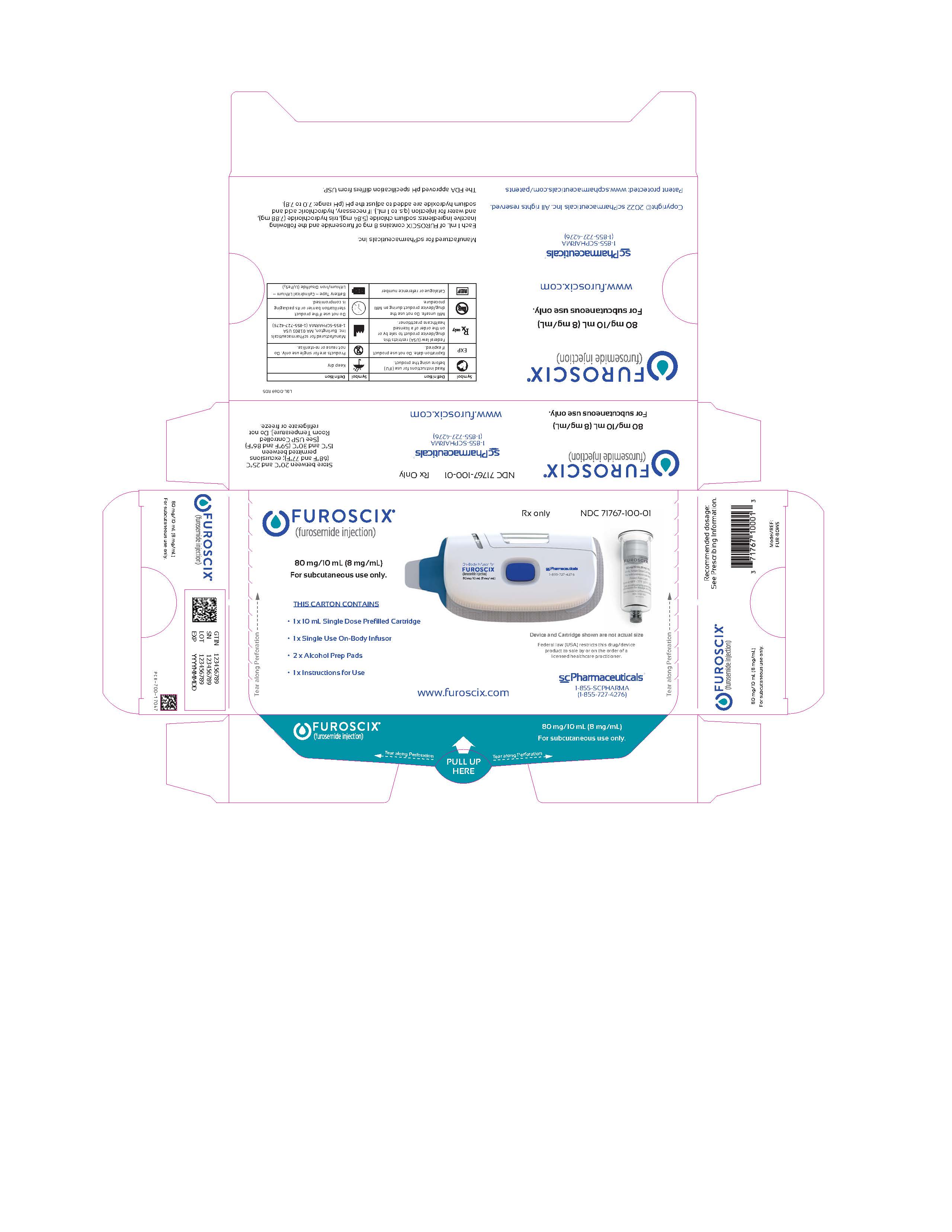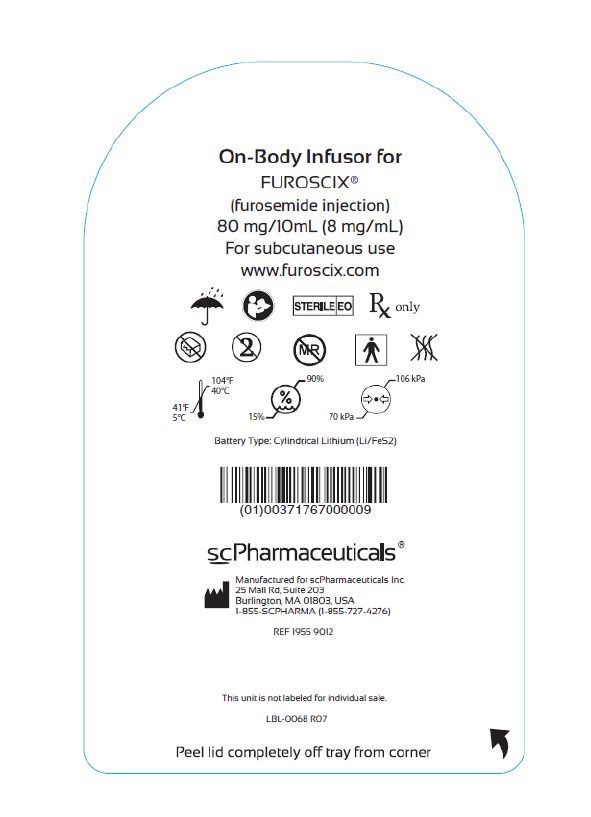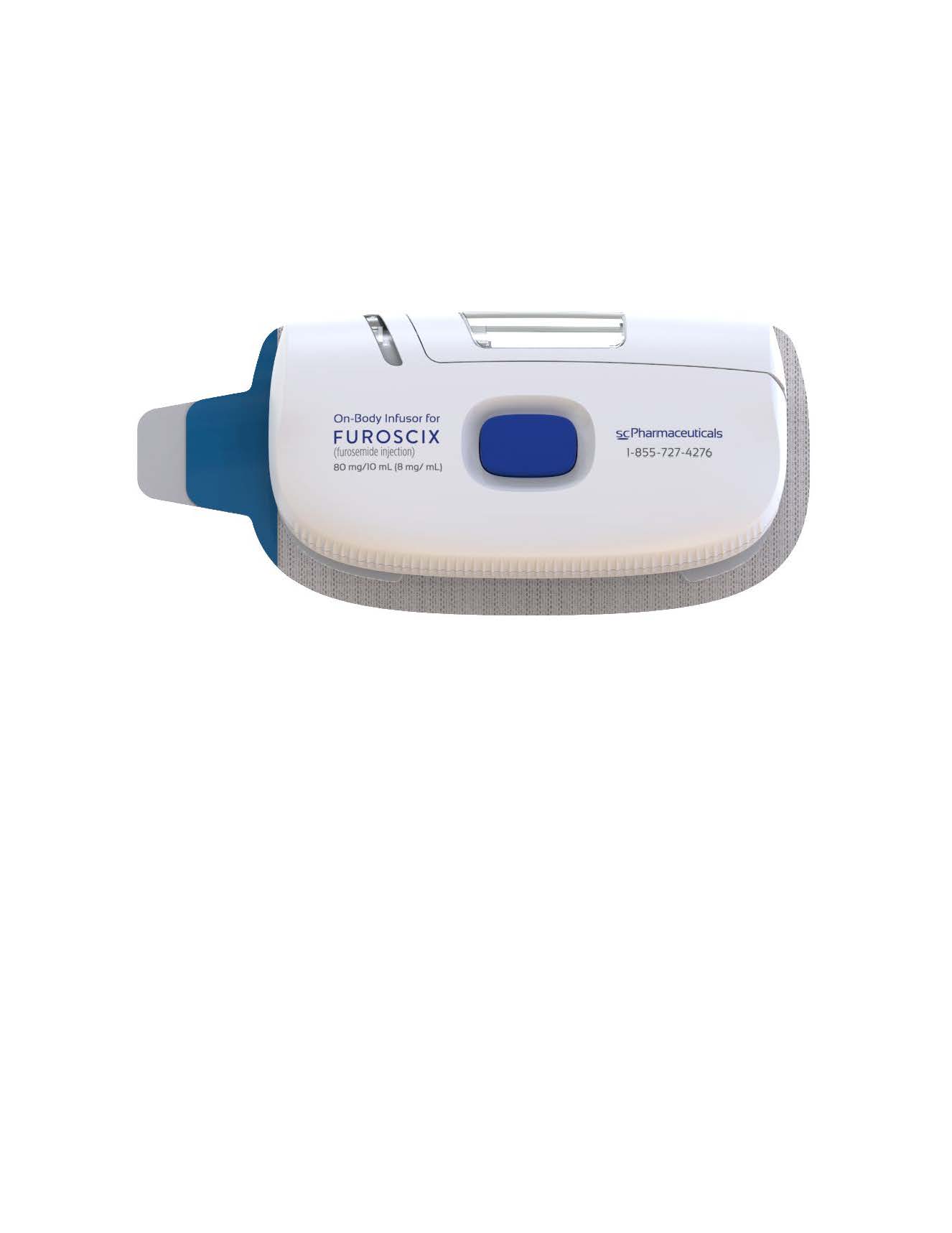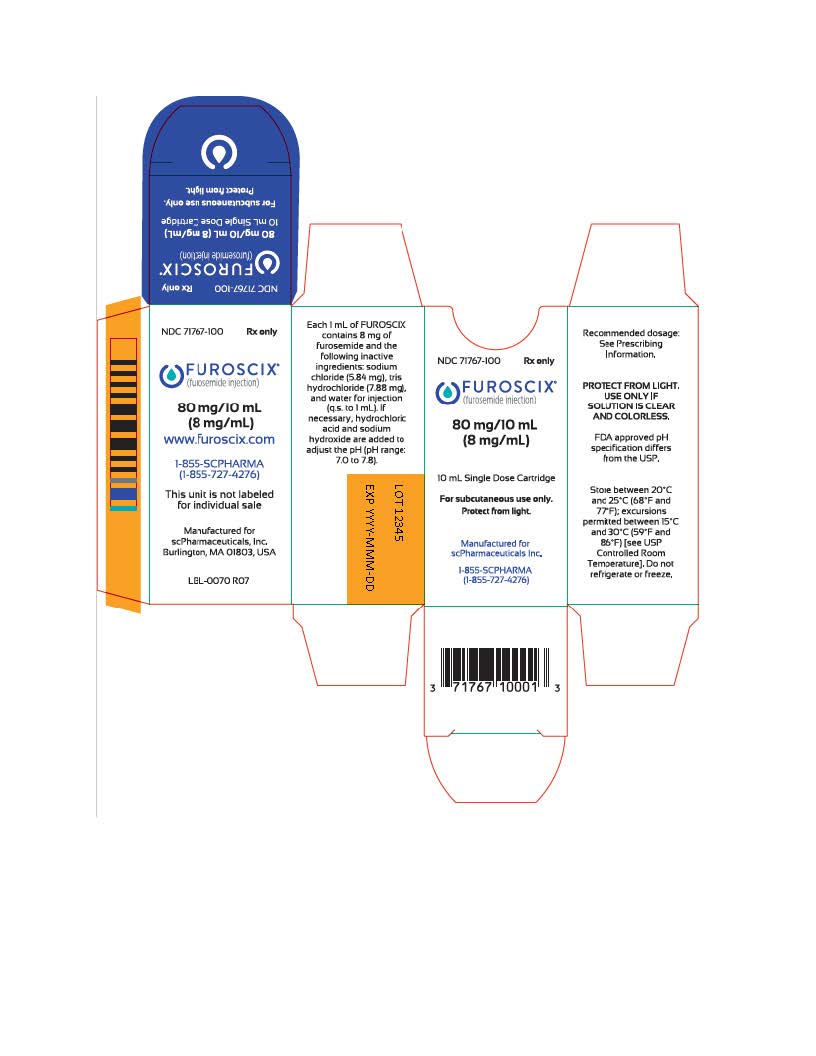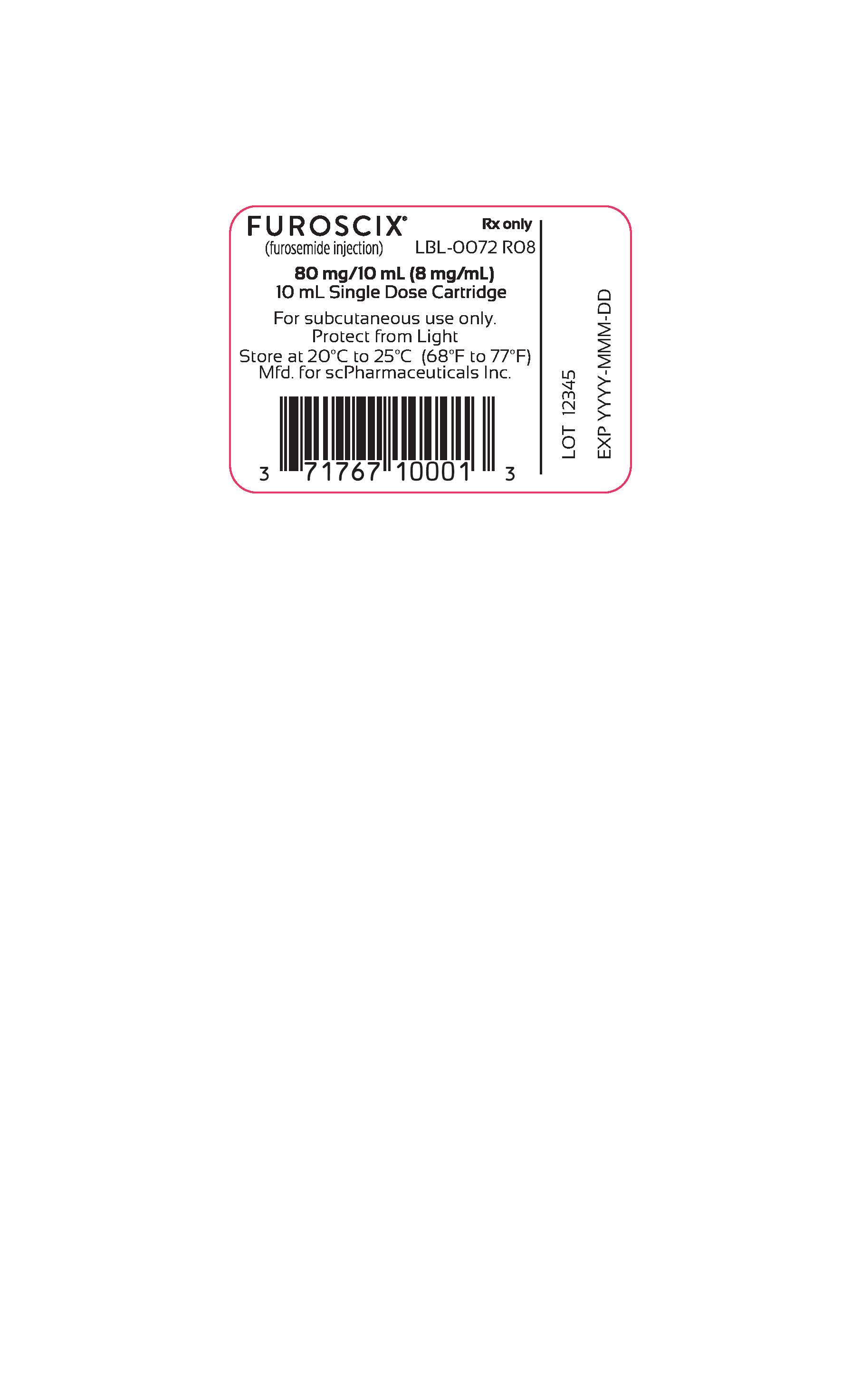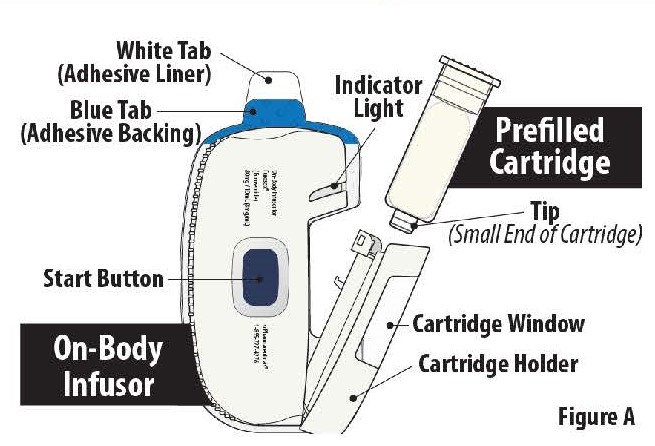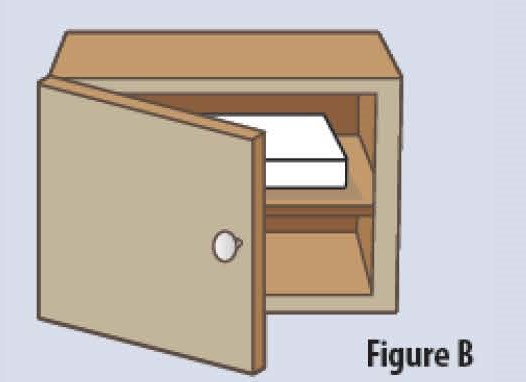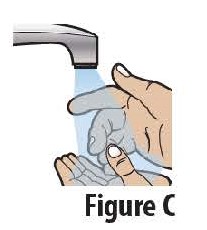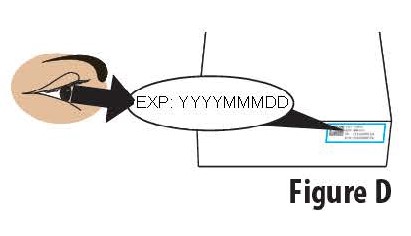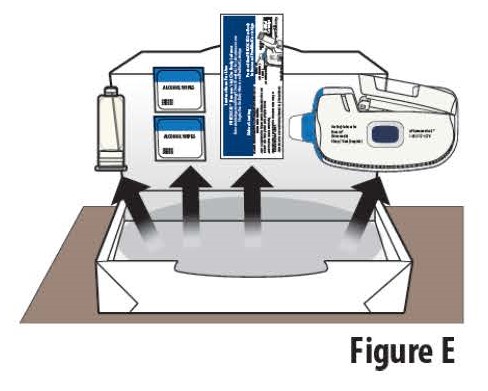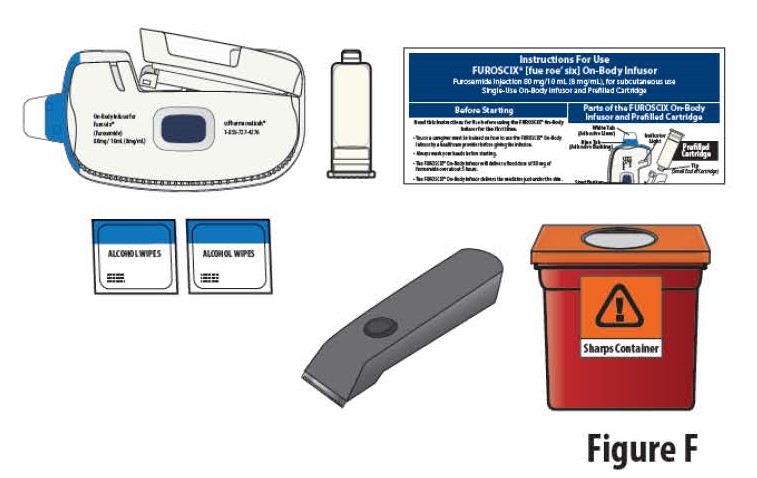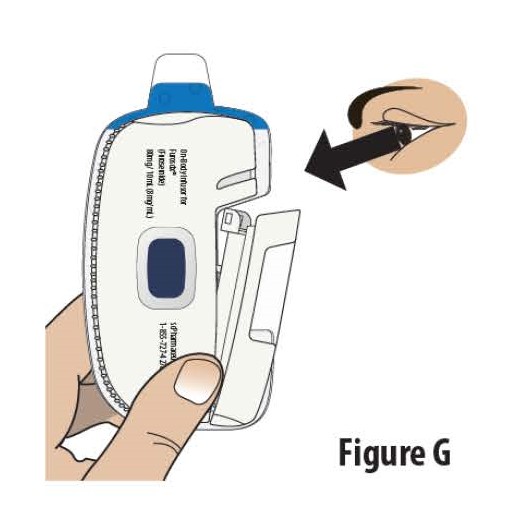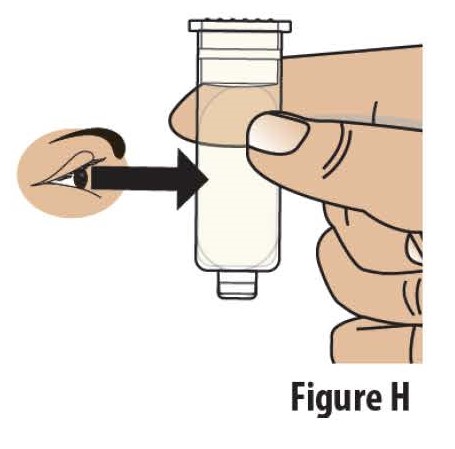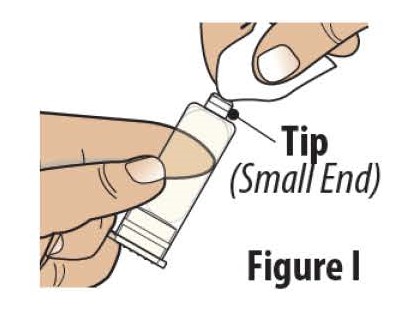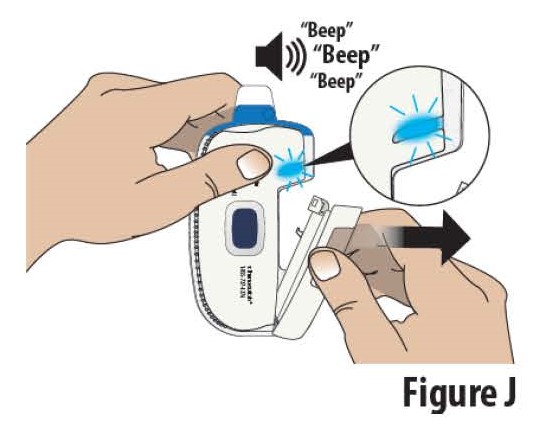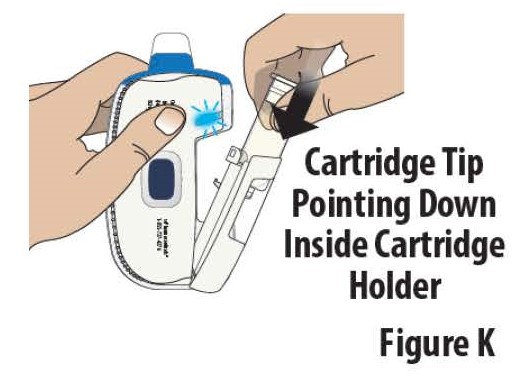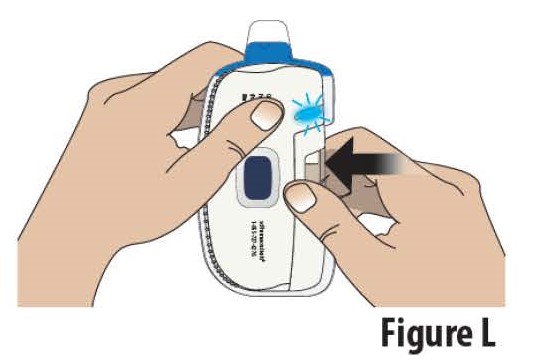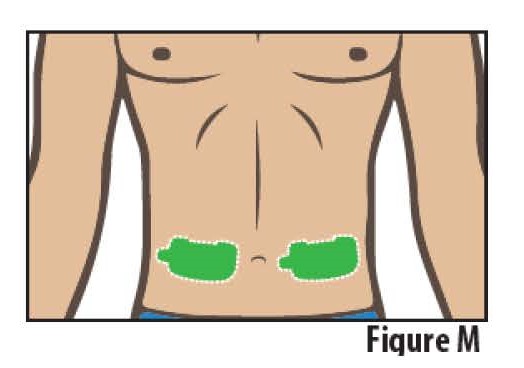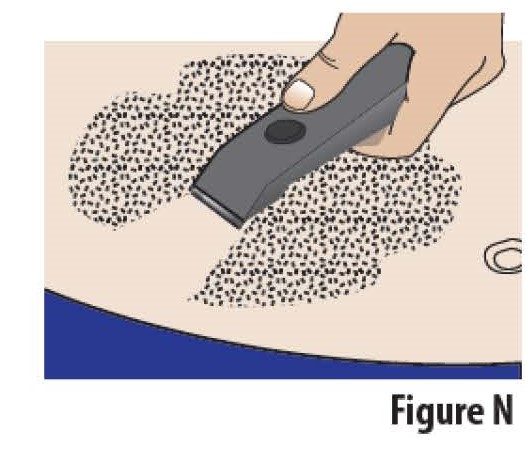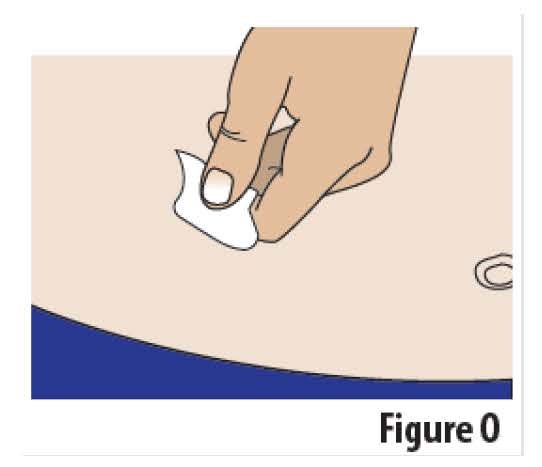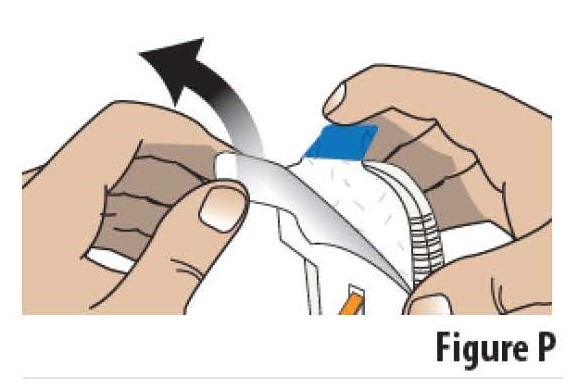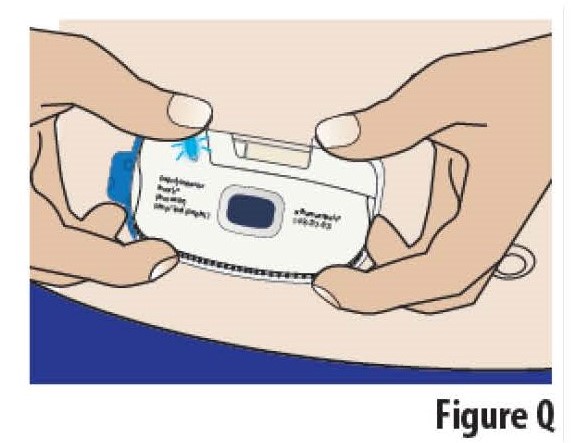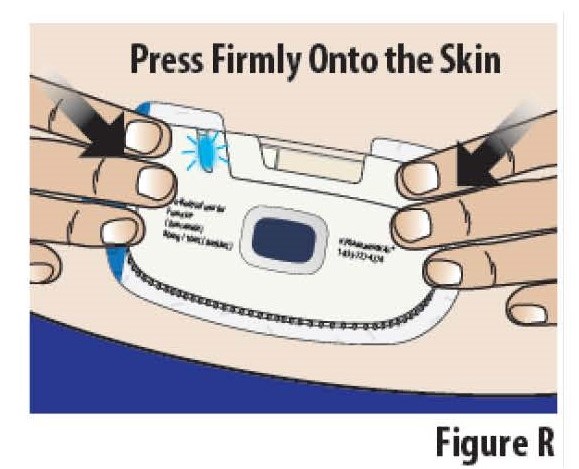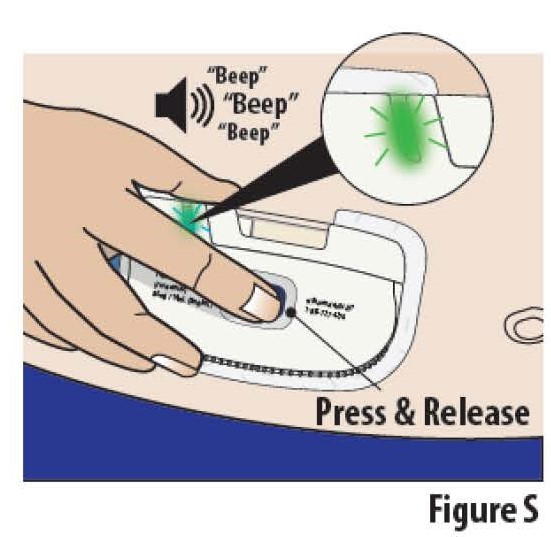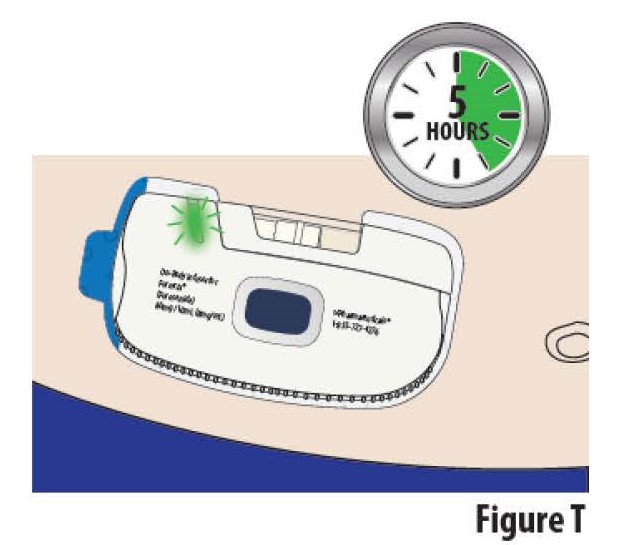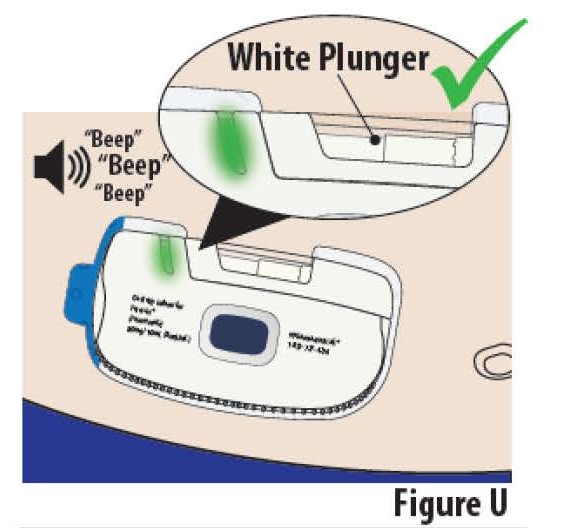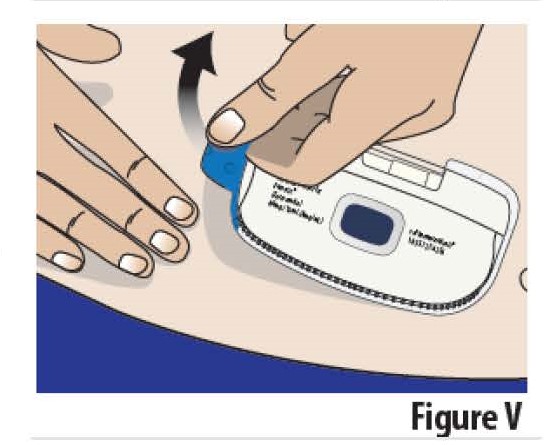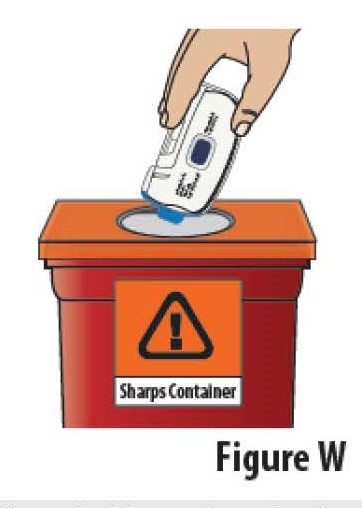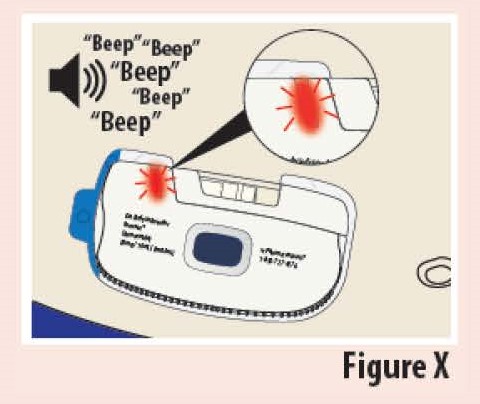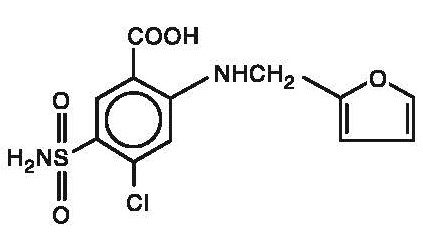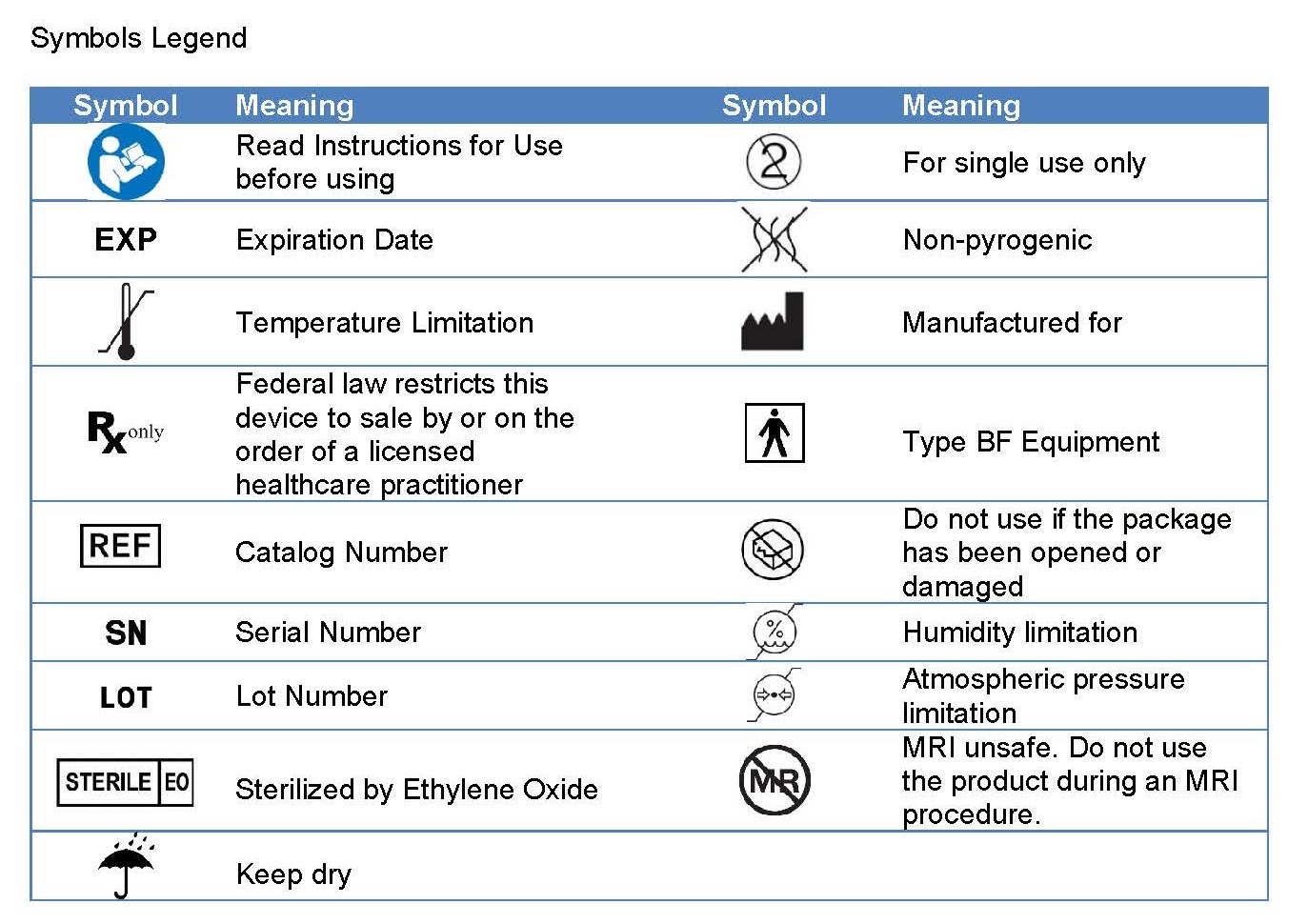 DRUG LABEL: FUROSCIX
NDC: 71767-100 | Form: INJECTION
Manufacturer: scPharmaceuticals Inc.
Category: prescription | Type: HUMAN PRESCRIPTION DRUG LABEL
Date: 20251223

ACTIVE INGREDIENTS: FUROSEMIDE 8 mg/1 mL

HIGHLIGHTS OF PRESCRIBING INFORMATION

These highlights do not include all the information needed to use FUROSCIX safely and effectively. See full prescribing information for FUROSCIX.
Furoscix® (furosemide injection), for subcutaneous use
Initial U.S. Approval: 1968

RECENT MAJOR CHANGES

Indications and Usage (1) 12/2025

Dosage and Administration (2.2) 12/2025

1 INDICATIONS AND USAGE

FUROSCIX is a loop diuretic indicated for the treatment of edema in pediatric patients weighing 43 kg and above and in adult patients with chronic heart failure or chronic kidney disease, including the nephrotic syndrome. (1)

2 DOSAGE AND ADMINISTRATION

- The single-use, On-body Infusor is pre-programmed to deliver 30mg of furosemide over the first hour then 12.5 mg per hour for the subsequent 4 hours. (2.1)
- FUROSCIX is not for chronic use and should be replaced with oral diuretics as soon as practical. (2.1)
- See Full Prescribing Information for important administration instructions. (2.2)

3 DOSAGE FORMS AND STRENGTHS

Injection: 80 mg/10 mL (8 mg/mL) in a single-dose prefilled cartridge co-packaged with a single-use On-body Infusor. (3)

4 CONTRAINDICATIONS

- Anuria (4)
- Hypersensitivity to furosemide, components of FUROSCIX formulation, or medical adhesives. (4)

5 WARNINGS AND PRECAUTIONS

- Fluid, Electrolyte, and Metabolic Abnormalities: Monitor serum electrolytes, CO2, BUN, creatinine, glucose, and uric acid. (5.1)
- Worsening Renal Function: Monitor for dehydration and azotemia. (5.2)
- Ototoxicity: Avoid higher than recommended doses. (5.3, 7.1)
- Acute Urinary Retention: Monitor patients with symptoms of urinary retention. (5.4)
- Incomplete Dosing: Fluid contact and certain patient movements during treatment may cause the On-body Infusor to prematurely terminate infusion. Ensure the patient or caregiver can detect and respond to alarms. (5.5)

6 ADVERSE REACTIONS

The most common adverse reactions during treatment with the Furoscix Infusor were administration site and skin reactions: erythema, bruising, edema and infusion site pain. (6)

To report SUSPECTED ADVERSE REACTIONS, contact scPharmaceuticals, Inc. at 1-855-727-4276 or FDA at 1-800-FDA-1088 or www.fda.gov/medwatch.

7 DRUG INTERACTIONS

- Aminoglycoside antibiotics: Increased potential ototoxicity of the antibiotics. Avoid combination. (7.1)
- Ethacrynic acid: Risk of ototoxicity. Avoid combination (7.1)
- Salicylates: Risk of salicylate toxicity. (7.1)
- Cisplatin and nephrotoxic drugs: Risk of ototoxicity and nephrotoxicity. (7.1)
- Lithium: Risk of lithium toxicity. (7.1)
- Renin-angiotensin inhibitors: Increased risk of hypotension and renal failure. (7.1)
- Adrenergic blocking drugs: Risk of potentiation. (7.1)
- Drugs undergoing renal tubular secretion: Risk of toxicity potentiation. (7.1)

See 17 for PATIENT COUNSELING INFORMATION .

FULL PRESCRIBING INFORMATION

1 INDICATIONS AND USAGE

FUROSCIX is indicated for the treatment of edema in pediatric patients weighing 43 kg and above and in adult patients adult patients with chronic heart failure or chronic kidney disease (CKD), including the nephrotic syndrome.

2 DOSAGE AND ADMINISTRATION

2.1 Recommended Dosage

The single-use, On-body Infusor with prefilled cartridge is pre-programmed to deliver 30 mg of furosemide over the first hour followed by 12.5 mg per hour for the subsequent 4 hours [see Use in Specific Populations (8.6) and see Clinical Pharmacology (12)].

FUROSCIX is not for chronic use and should be replaced with oral diuretics as soon as practical.

2.2 Important Administration Instructions

FUROSCIX is intended for use in a setting where the patient can limit their activity for the duration of administration. [see Warnings and Precautions (5.5)]

FUROSCIX is not compatible with use in an MRI setting.

Inspect FUROSCIX prefilled cartridge prior to administration. FUROSCIX is a clear to slightly yellow solution. Do not use FUROSCIX if solution is discolored or cloudy [see Description (11)] .

Refer to the Instructions for Use for additional information.

Load the prefilled cartridge of furosemide into the On-body Infusor and close the cartridge holder.

Peel away the adhesive liner on the On-body Infusor and apply onto a clean, dry area of the abdomen between the top of the beltline and the bottom of the ribcage that is not tender, bruised, red or indurated. The distance from the top of the beltline to the bottom of the ribcage should be at least 2 ½ inches.

Start the injection by firmly pressing and releasing the blue start button.

Do not remove until the injection is complete (signaled by the solid green status light, beeping sound, and the white plunger rod filling the cartridge window).

Rotate the site of each subcutaneous administration.

In pediatric patients weighing at least 43 kg, FUROSCIX must be administered by a healthcare provider or adult caregiver. Adult patients or caregivers should receive proper instruction in preparing and administering FUROSCIX before using the FUROSCIX On-body Infusor.

3 DOSAGE FORMS AND STRENGTHS

Injection: 80 mg/10 mL (8 mg/mL) as a clear to slightly yellow solution in a single-dose prefilled cartridge for use only with co-packaged single-use, On-body Infusor.

4 CONTRAINDICATIONS

FUROSCIX is contraindicated in:

- Patients with anuria
- Patients with a history of hypersensitivity to furosemide, any component of the FUROSCIX formulation, or medical adhesives.

5 WARNINGS AND PRECAUTIONS

5.1 Fluid, Electrolyte, and Metabolic Abnormalities

Furosemide may cause fluid, electrolyte, and metabolic abnormalities such as hypovolemia, hypokalemia, azotemia, hyponatremia, hypochloremic alkalosis, hypomagnesemia, hypocalcemia, hyperglycemia, or hyperuricemia, particularly in patients receiving higher doses, patients with inadequate oral electrolyte intake, and in elderly patients. Excessive diuresis may cause dehydration and blood volume reduction with circulatory collapse and possibly vascular thrombosis and embolism, particularly in elderly patients. Serum electrolytes, CO2, BUN, creatinine, glucose, and uric acid should be monitored frequently during furosemide therapy [see Use in Specific Populations (8.6)] .

5.2 Worsening Renal Function

Furosemide can cause dehydration and azotemia. If increasing azotemia and oliguria occur during treatment of severe progressive renal disease, discontinue furosemide [see Clinical Pharmacology (12.3)].

5.3 Ototoxicity

Cases of tinnitus and reversible or irreversible hearing impairment and deafness have been reported with furosemide. Reports usually indicate that furosemide ototoxicity is associated with rapid injection, severe renal impairment, the use of higher than recommended doses, hypoproteinemia or concomitant therapy with aminoglycoside antibiotics, ethacrynic acid, or other ototoxic drugs. If the physician elects to use high-dose parenteral therapy, controlled intravenous infusion is advisable (for adults, an infusion rate not exceeding 4 mg furosemide per minute has been used) [see Drug Interactions (7.1)].

5.4 Acute Urinary Retention

In patients with severe symptoms of urinary retention (because of bladder emptying disorders, prostatic hyperplasia, urethral narrowing), the administration of furosemide can cause acute urinary retention related to increased production and retention of urine. These patients require careful monitoring, especially during the initial stages of treatment.

5.5 Incomplete Dosing

The On-body Infusor should not be allowed to get wet from water or any other fluids (blood or drug product). Fluid contact with the circuit board can lead to device errors and premature termination of infusion.

The On-body Infusor is intended for use in a setting where the patient can limit their activity for the duration of administration. Certain patient movements may cause interruption of device adherence to skin and premature termination of infusion.

The On-body Infusor for FUROSCIX should only be administered in settings where alarms can be detected and responded to in order to ensure a complete dose is administered [see Dosage and Administration (2.2)].

6 ADVERSE REACTIONS

The following important adverse reactions are discussed elsewhere in the labeling:

- Fluid, Electrolyte, and Metabolic Abnormalities [see Warnings and Precautions (5.1)].
- Ototoxicity [see Warnings and Precautions (5.3)]

The following adverse reactions associated with the use of furosemide were identified in clinical trials or post-marketing reports. Because these reactions were reported voluntarily from a population of uncertain size, it is not always possible to estimate their frequency reliably, or to establish a causal relationship to drug exposure.

Adverse reactions are categorized below by organ system and listed by decreasing severity.

Gastrointestinal System Reactions: pancreatitis, jaundice (intrahepatic cholestatic jaundice), increased liver enzymes, anorexia, oral and gastric irritation, cramping, diarrhea, constipation, nausea, vomiting.

Systemic Hypersensitivity Reactions: severe anaphylactic or anaphylactoid reactions (e.g., with shock), systemic vasculitis, interstitial nephritis, necrotizing angiitis.

Central Nervous System Reactions: tinnitus and hearing loss, paresthesias, vertigo, dizziness, headache, blurred vision, xanthopsia.

Hematologic Reactions: aplastic anemia, thrombocytopenia, agranulocytosis, hemolytic anemia, leukopenia, anemia, eosinophilia.

Dermatologic Hypersensitivity Reactions: toxic epidermal necrolysis, Stevens-Johnson Syndrome, erythema multiforme, drug rash with eosinophilia and systemic symptoms, acute generalized exanthematous pustulosis, exfoliative dermatitis, bullous pemphigoid, purpura, photosensitivity, rash.

Cardiovascular Reactions: orthostatic hypotension, increase in cholesterol and triglyceride serum levels.

Administration Site and Skin Reactions: erythema, bruising, edema, infusion site pain.

Other Reactions: glycosuria, muscle spasm, weakness, restlessness, urinary bladder spasm, thrombophlebitis, transient injection site pain following intramuscular injection, fever.

7 DRUG INTERACTIONS

7.1 Effects of Furosemide on Other Drugs

Drug/Substance Class or Name | Drug Interaction Effect | Recommendations
Aminoglycoside antibiotics | Furosemide may increase the ototoxic potential of aminoglycoside antibiotics, especially in the presence of impaired renal function [see Warnings and Precautions (5.3)]. | Avoid combination except in life-threatening situations.
Ethacrynic acid | Possibility of ototoxicity [see Warnings and Precautions (5.3)]. | Avoid concomitant use with ethacrynic acid.
Salicylates | May experience salicylate toxicity at lower doses because of competitive renal excretory sites. | Monitor for symptoms of salicylate toxicity.
Cisplatin | There is a risk of ototoxic effects if cisplatin and furosemide are given concomitantly [see Warnings and Precautions (5.3)].
Cisplatin and nephrotoxic drugs | Nephrotoxicity | Administer furosemide at lower doses and with positive fluid balance when used to achieve forced diuresis during cisplatin treatment. Monitor renal function.
Paralytic agents | Furosemide has a tendency to antagonize the skeletal muscle relaxing effect of tubocurarine and may potentiate the action of succinylcholine. | Monitor for skeletal muscle effect.
Lithium | Furosemide reduces lithium’s renal clearance and add a high-risk of lithium toxicity. | Avoid concomitant use with lithium.
Angiotensin converting enzyme inhibitors or angiotensin II receptor blockers | May lead to severe hypotension and deterioration in renal function, including renal failure. | Monitor for changes in blood pressure and renal function and interrupt or reduce the dosage of furosemide, angiotensin converting enzyme inhibitors, or angiotensin receptor blockers if needed.
Antihypertensive drugs | Furosemide may add to or potentiate the therapeutic effect of other antihypertensive drugs. | Monitor for changes in blood pressure and adjust the dose of other antihypertensive drugs if needed.
Adrenergic blocking drugs or peripheral adrenergic blocking drugs | Potentiation occurs. | Monitor for changes in blood pressure and adjust the dose of adrenergic blocking drugs if needed.
Norepinephrine | Furosemide may decrease arterial responsiveness (vasoconstricting effect) to norepinephrine. | Monitor blood pressure (or mean arterial pressure).
Chloral hydrate | In isolated cases, intravenous administration of furosemide within 24 hours of taking chloral hydrate may lead to flushing, sweating attacks, restlessness, nausea, increase in blood pressure, and tachycardia. | Concomitant use with chloral hydrate is not recommended.
Methotrexate and other drugs undergoing renal tubular secretion | Furosemide may decrease renal elimination of other drugs that undergo tubular secretion. High-dose treatment of furosemide may result in elevated serum levels of these drugs and may potentiate their toxicity. | Monitor serum levels of drugs undergoing renal tubular secretion and adjust the dose if needed.
Cephalosporin | Furosemide can increase the risk of cephalosporin-induced nephrotoxicity even in the setting of minor or transient renal impairment. | Monitor for changes in renal function.
Cyclosporine | Increased risk of gouty arthritis secondary to furosemide-induced hyperuricemia and cyclosporine impairment of renal urate excretion. | Monitor serum urate levels.
Thyroid hormones | High-doses (> 80 mg) of furosemide may inhibit the binding of thyroid hormones to carrier proteins and result in transient increase in free thyroid hormones, followed by an overall decrease in total thyroid hormone levels. | Monitor the total thyroid hormone levels.

7.2 Effect of Other Drugs on Furosemide

Drug/Substance Class or Name | Drug Interaction Effect | Recommendations
Phenytoin | Phenytoin interferes directly with renal action of furosemide. | Monitor diuretic effects of furosemide and adjust the dose of furosemide if needed.
Methotrexate and other drugs undergoing renal tubular secretion | May reduce the effect of furosemide. High-dose treatment of methotrexate and these other drugs may result in elevated serum levels of furosemide and may potentiate the toxicity of furosemide. | Monitor for enhanced toxicity of furosemide.
Indomethacin | Coadministration of indomethacin may reduce the natriuretic and antihypertensive effects of furosemide in some patients by inhibiting prostaglandin synthesis. Indomethacin may also affect plasma renin levels, aldosterone excretion, and renin profile evaluation. | Patients receiving both indomethacin and furosemide should be observed closely to determine if the desired diuretic and/or antihypertensive effect of furosemide is achieved.

8 USE IN SPECIFIC POPULATIONS

8.1 Pregnancy

Risk Summary

Available data from published observational studies, case reports, and post marketing reports, from decades of use, have not demonstrated a drug-associated risk of major birth defects, miscarriage, or other adverse maternal or fetal outcomes with furosemide use during pregnancy. Untreated congestive heart failure and cirrhosis of the liver can lead to adverse outcomes for the mother and the fetus (see Clinical Considerations).

In animal reproduction studies, furosemide has been shown to cause unexplained maternal deaths and abortions in rabbits when administered orally during organogenesis at 4 times a human i.v. dose of 80 mg based on body surface area (BSA) and oral bioavailability corrections, presumably secondary to volume depletion (see Data).

The estimated background risk for major birth defects and miscarriage for the indicated populations is unknown. All pregnancies have a background risk of birth defect, loss, or other adverse outcomes. In the U.S. general population, the estimated background risk of major birth defects and miscarriage in the clinically recognized pregnancies is 2 to 4% and 15 to 20%, respectively.

Clinical Considerations

Disease-associated Maternal and/or Embryo/fetal Risk

Pregnant women with congestive heart failure are at increased risk for pre-term birth. Stroke volume and heart rate increase during pregnancy, increasing cardiac output, especially during the first trimester. Clinical classification of heart disease may worsen with pregnancy and lead to maternal death and/or stillbirth. Closely monitor pregnant patients for destabilization of their heart failure.

Pregnant women with symptomatic cirrhosis generally have poor outcomes including hepatic failure, variceal hemorrhage, pre-term delivery, fetal growth restriction and maternal death. Outcomes are worse with coexisting esophageal varices. Carefully monitor pregnant women with cirrhosis of the liver.

Data

Animal Data

The effects of furosemide on embryonic and fetal development and on pregnant dams were studied in mice, rats, and rabbits.

Furosemide caused unexplained maternal deaths and abortions in the rabbit at the lowest dose of 25 mg/kg (approximately 4 times the human i.v. dose of 80 mg based on BSA and oral bioavailability corrections). In another study, a dose of 50 mg/kg (approximately 7 times a human i.v. dose of 80 mg based on BSA and oral bioavailability corrections) also caused maternal deaths and abortions when administered to rabbits between Days 12 and 17 of gestation. In a third study, none of the pregnant rabbits survived an oral dose of 100 mg/kg. Data from the above studies indicate fetal lethality that can precede maternal deaths.

The results of the mouse study and one of the three rabbit studies also showed an increased incidence and severity of hydronephrosis (distention of the renal pelvis and, in some cases, of the ureters) in fetuses of treated dams as compared with the incidence of fetuses from the control group.

8.2 Lactation

Risk Summary

The presence of furosemide has been reported in human breast milk. There are no data on the effects on the breastfed infant or the effects on milk production. Doses of furosemide associated with clinically significant diuresis may impair milk production. The developmental and health benefits of breastfeeding should be considered along with the mother’s clinical need for furosemide and any potential adverse effects on the breastfed infant from furosemide or from the underlying maternal condition.

8.4 Pediatric Use

FUROSCIX is approved for the treatment of edema in pediatric patients weighing at least 43 kg with chronic heart failure or chronic kidney disease, including the nephrotic syndrome. FUROSCIX has not been studied in pediatric patients. Use of FUROSCIX for this indication is supported by: 1) efficacy, safety, and pharmacokinetic data of furosemide in adult and pediatric patients; 2) pharmacokinetic and pharmacodynamic data of FUROSCIX in adults with New York Heart Association (NYHA) Functional Classification Class II and Class III heart failure [see Clinical Pharmacology (12.2, 12.3)] ; and 3) population pharmacokinetic modeling which demonstrated no significant difference in furosemide exposure following FUROSCIX administration in a simulated pediatric population weighing 43 kg and above and aged 6 to <17 years compared to adult patients with chronic heart failure [see Clinical Pharmacology (12.3)].

FUROSCIX is not approved for the treatment of edema in pediatric patients weighing less than 43 kg.

8.5 Geriatric Use

Controlled clinical studies did not include sufficient numbers of subjects to determine whether subjects aged 65 and over respond differently from younger subjects. Other reported clinical experience has not identified differences in responses between the elderly and younger patients. In general, dose selection for the elderly patients should be cautious, reflecting the greater frequency of decreased hepatic, renal or cardiac function, and of concomitant disease or other drug therapy.

FUROSCIX is known to be substantially excreted by the kidney, and the risk of toxic reactions to this drug may be greater in patients with impaired renal function. Because elderly patients are more likely to have decreased renal function, care should be taken in dose selection, and it may be useful to monitor renal function [see Clinical Pharmacology (12.3)].

8.6 Renal Impairment

Significantly reduced renal function can affect the response to furosemide. The On-body Infusor will deliver only an 80 mg dose of furosemide, and patients with significantly reduced renal function may require additional diuretic therapy.

8.7 Hepatic Impairment

In patients with hepatic cirrhosis and ascites, sudden alterations of fluid and electrolyte balance may precipitate hepatic encephalopathy and coma. Treat such patients in a setting where clinical status and electrolyte balance can be carefully monitored.

10 OVERDOSAGE

The principal signs and symptoms of overdose with FUROSCIX are dehydration, blood volume reduction, hypotension, electrolyte imbalance, hypokalemia and hypochloremic alkalosis, and are extensions of its diuretic action.

The concentration of furosemide in biological fluids associated with toxicity or death is not known.

Treatment of overdosage is supportive and consists of replacement of excessive fluid and electrolyte losses. Serum electrolytes, carbon dioxide level and blood pressure should be determined frequently. Adequate drainage must be assured in patients with urinary bladder outlet obstruction (such as prostatic hypertrophy).

Hemodialysis does not accelerate furosemide elimination.

11 DESCRIPTION

FUROSCIX (furosemide injection 80 mg/10 mL) is a loop diuretic which is an anthranilic acid derivative.

Chemically, it is 4-chloro-N-furfuryl-5-sulfamoylanthranilic acid.

Furosemide is a white to slightly yellow crystalline powder. It is sparingly soluble in alcohol, freely soluble in dilute alkali solutions and insoluble in dilute acids. The structural formula is as follows:

Molecular Formula: C12H11ClN2O5S

Molecular Weight: 330.75 g/mol

FUROSCIX is a single-dose prefilled cartridge co-packaged with a single-use, On-body Infusor. The single-dose prefilled cartridge contains 80 mg per 10 mL sterile, clear to slightly yellow, and non-pyrogenic furosemide solution. The pH of FUROSCIX, 7.4, differs from that of Furosemide Injection, USP.

Each 1 mL of FUROSCIX contains the following inactive ingredients: hydrochloric acid for pH adjustment if needed, sodium chloride (5.84 mg), sodium hydroxide for pH adjustment if needed, tris HCl (7.88 mg), and water for injection (q.s.).

FUROSCIX is administered via a wearable, single-use, electromechanical (battery powered, micro-processor controlled), On-body delivery system that is pre-programmed to deliver 80 mg of FUROSCIX over 5-hours using a bi-phasic delivery profile.

12 CLINICAL PHARMACOLOGY

12.1 Mechanism of Action

Furosemide primarily inhibits the reabsorption of sodium and chloride in the proximal and distal tubules and in the loop of Henle. The high degree of diuresis is largely due to the unique site of action. The action on the distal tubule is independent of any inhibitory effect on carbonic anhydrase and aldosterone.

12.2 Pharmacodynamics

In adult patients with NYHA Class II and Class III heart failure, subcutaneous administration of FUROSCIX (30 mg furosemide over the first hour followed by 12.5 mg per hour for the subsequent 4 hours, total 80mg furosemide) produced similar diuresis and natriuresis to intravenous administration (two 40 mg bolus doses separated by 120 minutes) at 8 and 24 hour post-dose. The duration of diuretic effect with FUROSCIX is up to 8 hours after initiation of dosing.

12.3 Pharmacokinetics

Absorption

In adult patients with NYHA Class II-III congestive heart failure, subcutaneous infusion of FUROSCIX (30 mg furosemide over the first hour followed by 12.5 mg per hour for the subsequent 4 hours, 80 mg furosemide total), the bioavailability was 99.6% (90% CI: 94.8, 104.8) with a median Tmax of 4 hours relative to 80 mg intravenous furosemide (two 40-mg bolus doses separated by 120 minutes). The pharmacokinetic parameters of FUROSCIX are presented in Table 1 below:

Table 1: Pharmacokinetic Data of FUROSCIX Following Subcutaneous Infusion (n = 15)

Dose | Cmax; (ng/mL) | AUCt (ng×hr/mL) | T1/2 (hr) | AUC∞; (ng×hr/mL)
FUROSCIX: 30 mg subcutaneously infused over the first hour followed by 12.5 mg per hour for the subsequent 4 hours (total dose: 80 mg furosemide) | 2040 ± 449 | 13000 ± 4000 | 3.2 ± 0.9 | 13100 ± 4010
Furosemide administered as 2 x 40 mg bolus doses intravenously, separated by 120 minutes (total dose: 80 mg furosemide) | 8580 ± 2540 | 13000 ± 4050 | 2.6 ± 0.3 | 13200 ± 4170

The impact of subcutaneous edema at the administration site of FUROSCIX on drug absorption is unknown.

Distribution

Furosemide is extensively bound to plasma proteins, mainly to albumin. Plasma concentrations ranging from 1 mcg per mL to 400 mcg per mL are 91% to 99% bound in healthy individuals. The unbound fraction averages 2.3% to 4.1% at therapeutic concentrations.

Elimination

The terminal half-life of furosemide is approximately 2 hours.

Metabolism

Furosemide glucuronide is the only or at least the major biotransformation product of furosemide in humans.

Excretion

Significantly more furosemide is excreted in urine following the intravenous injection than after the tablet or oral solution.

Specific Populations

Pediatric Patients

FUROSCIX was not evaluated in a pediatric clinical study. Based on population pharmacokinetic modeling and simulation, pediatric patients aged 6 to <17 years and weighing 43 kg and above are predicted to have comparable exposures to adult patients following FUROSCIX administration.

Geriatric Patients

Furosemide binding to albumin may be reduced in elderly patients. Furosemide is predominantly excreted unchanged in the urine. The renal clearance of furosemide after intravenous administration in older healthy male subjects (60 to 70 years of age) is significantly less than in younger healthy male subjects (20 to 35 years of age). The initial diuretic effect of furosemide in older subjects is decreased relative to younger subjects [see Use in Specific Populations (8.5)] .

13 NONCLINICAL TOXICOLOGY

13.1 Carcinogenesis, Mutagenesis, Impairment of Fertility

Carcinogenesis

Furosemide was tested for carcinogenicity by oral administration in one strain of mice and one strain of rats. A small but significantly increased incidence of mammary gland carcinomas occurred in female mice at a dose approximately 8 times a human i.v. dose of 80 mg based on BSA and oral bioavailability corrections. There were marginal increases in uncommon tumors in male rats at a dose of 15 mg per kg (slightly greater than the maximum human dose) but not at 30 mg per kg.

Mutagenesis

Furosemide was devoid of mutagenic activity in various strains of Salmonella typhimurium when tested in the presence or absence of an in vitro metabolic activation system, and questionably positive for gene mutation in mouse lymphoma cells in the presence of rat liver S9 at the highest dose tested. Furosemide did not induce sister chromatid exchange in human cells in vitro, but other studies on chromosomal aberrations in human cells in vitro gave conflicting results. In Chinese hamster cells it induced chromosomal damage but was questionably positive for sister chromatid exchange. Studies on the induction by furosemide of chromosomal aberrations in mice were inconclusive. The urine of rats treated with this drug did not induce gene conversion in Saccharomyces cerevisiae.

Impairment of Fertility

Furosemide produced no impairment of fertility in male or female rats, at 100 mg per kg per day (the maximum effective diuretic dose in the rat), approximately 7 times a human i.v. dose of 80 mg based on BSA and oral bioavailability corrections.

16 HOW SUPPLIED/STORAGE AND HANDLING

FUROSCIX injection is a sterile, clear to slightly yellow, non-pyrogenic liquid supplied in a single-dose prefilled cartridge for subcutaneous infusion co-packaged with the On-body Infusor. Each single-use On-body Infusor with prefilled cartridge is designed to deliver 80 mg of FUROSCIX in 10 mL solution over 5-hours.

Carton containing one 80 mg/10 mL (8 mg/mL) prefilled cartridge co-packaged with one On-body Infusor | NDC 71767-100-01

Store between 20°C and 25°C (68°F and 77°F); excursions permitted between 15°C and 30°C (59°F and 86°F) [See USP Controlled Room Temperature]. Do not refrigerate or freeze.

Protect FUROSCIX from light. Do not remove the cartridge from carton until it is ready for use. Do not use if the solution is discolored or cloudy. Protect the On-body Infusor from water.

17 PATIENT COUNSELING INFORMATION

Advise the patient and/or caregiver to read the FDA-approved patient labeling [see FDA-approved Instructions for Use].

Advise the patient that they should not allow the On-body Infusor to come into contact with water or other fluids.Advise patients and/or caregiver to check the device for alarms to ensure a complete dose is administered [see Warnings and Precautions (5.5)] .

Fluid, Electrolyte, and Metabolic Abnormalities

Advise patients that they may experience symptoms from excessive fluid and/or electrolyte losses. The postural hypotension that sometimes occurs can usually be managed by getting up slowly. Potassium supplements and/or dietary measures may be needed to control or avoid hypokalemia [see Warnings and Precautions (5.1)] .

Advise patients that furosemide may increase blood glucose levels and thereby affect urine glucose tests [see Warnings and Precautions (5.1)].

Photosensitivity

The skin of some patients may be more sensitive to the effects of sunlight while taking furosemide [see Adverse Reactions (6)] .

Advise hypertensive patients to avoid medications that may increase blood pressure, including over-the-counter products for appetite suppression and cold symptoms [see Drug Interactions (7.1)] .

For more information about FUROSCIX, go to www.FUROSCIX.com or call 1-855-SCPHARMA (1-855-727-4276)

scPharmaceuticals, Inc.

FUROSCIX® (furosemide injection 80 mg/10 mL) for subcutaneous use

Manufactured for:

scPharmaceuticals Inc.,

25 Mall Road, Suite 203,

Burlington, MA 01803

Patent Protected: www.scpharmaceuticals.com/patents

FUROSCIX® is a mark of scPharmaceuticals Inc.

Reg-0018 Rev 04

INSTRUCTIONS FOR USE

Model/REF # FUR-80W5

Instructions For Use

On-Body Infusor for

FUROSCIX® [fue roe’ six]

(furosemide injection) for subcutaneous use

Single-Use On-Body Infusor and

80 mg/10 mL (8 mg/mL) Prefilled Cartridge

This Instructions for Use contains information about how to prepare and use FUROSCIX On-Body Infusor.

Before Starting

- Read this Instructions for Use before using the FUROSCIX On-Body Infusor for the first time.
- You or a caregiver should receive training before using the Furoscix On-Body Infusor.
- Always wash your hands before starting.
- The FUROSCIX On-Body Infusor will deliver a fixed dose of 80 mg of furosemide over about 5 hours.
- The FUROSCIX On-Body Infusor delivers the medicine just under the skin (subcutaneously).
- When the FUROSCIX On-Body Infusor is started, a small needle sticks into the skin to deliver the medicine. The on-body Infusor signals when all the medicine has been delivered. When the on-body Infusor is removed from the skin, a needle cover will extend over the needle to protect from an accidental needle stick.

Parts of the FUROSCIX On-Body Infusor and Prefilled Cartridge

Important Information

- The on-body Infusor and prefilled cartridge are not made with natural rubber latex.
- The infusion will last about 5 hours. During this time, you should limit your activity so that your bending movements are limited. Wearing the Infusor while riding in a car or flying in an airplane is not recommended.
- You should notice an increase in urine production in about an hour after the infusion is started and may need to make frequent bathroom visits. Be sure you have access to a bathroom for up to 8 hours after starting the infusion. If you do not notice the need to go to the bathroom, call your healthcare provider.
- The on-body Infusor can only be used with the prefilled FUROSCIX cartridge supplied in the kit.
- Do not use any other cartridges or medicines inside the on-body Infusor.
- Do not apply lotions, oils, or ointments to the adhesion area of the abdomen prior to applying the on-body Infusor to the abdomen.
- Do not use the on-body Infusor if the packaging appears to be opened, or if the on-body Infusor has been dropped or appears to be broken or damaged.
- Do not use the on-body Infusor within 12 inches of mobile phones, tablets, computers or wireless accessories (for example: TV remote control, Bluetooth computer keyboard or mouse).
- Do not use the on-body Infusor or prefilled cartridge after the expiration date on the carton.
- Do not use the prefilled cartridge if the liquid is discolored or cloudy. The liquid in the prefilled cartridge should be clear to slightly yellow in color.
- Do not use the on-body Infusor in or around an MRI machine.
- Do not take the on-body Infusor off your skin while it is infusing, unless there is an emergency or a device error. Removing the on-body Infusor before the infusion is done will result in a partial dose. The on-body Infusor will stop infusing and it cannot be restarted. Do not apply a new on-body Infusor unless instructed to do so by your healthcare provider.
- Do not reuse the on-body Infusor. The on-body Infusor is for single use only.
- Do not let the on-body Infusor get wet from water or any other liquids. Do not shower, bathe, swim or do activities that may make you sweat while wearing the on-body Infusor. It contains parts that should not get wet.

Call your healthcare provider or scPharmaceuticals at 1-855-SCPHARMA (1-855-727-4276) if you have any questions.

Storage Information

- The FUROSCIX On-Body Infusor and prefilled cartridge should be stored at controlled room temperature between 68°F to 77°F (20°C to 25°C) (see Figure B). Do not refrigerate or freeze.
- Keep the FUROSCIX prefilled cartridge in the original carton to protect from light or physical damage until you are ready to use.
- Keep the FUROSCIX On-Body Infusor and prefilled cartridge out of the reach of children.

Prepare for the Infusion

STEP 1 Wash Hands, Check Expiration Date and Remove Supplies from Carton

1.1 Wash your hands before using the on-body Infusor (Figure C).

1.2 Check the expiration date on the FUROSCIX On-Body Infusor carton (see Figure D). Do not use if the expiration date has passed.

1.3 Open the carton and peel away the white paper cover. Remove the plastic cover from the clear tray. Remove supplies from the carton and packaging (see Figure E). Do not use the on-body Infusor or prefilled cartridge if packaging appears to have been previously opened or damaged.

1.4 Gather all materials needed for your injection, on a clean, well-lit work surface (Figure F):

- On-body Infusor and prefilled cartridge (Included)
- Instructions For Use (Included)
- Alcohol wipes (Included)
- Clippers (if needed) (Not included)
- Sharps disposal container (Not included)

STEP 2 Check On-Body Infusor and Prefilled Cartridge

2.1 Check the on-body Infusor and prefilled cartridge for any damage (see Figure G).

Do not use the on-body Infusor or prefilled cartridge if either item appears to be damaged.

Do not touch the blue start button until the on-body Infusor is on the skin and you are ready to begin the infusion.

Do not touch or fully open the cartridge holder until you are ready to load the cartridge.

2.2 Check the liquid medicine in the prefilled cartridge (see Figure H). The liquid in the prefilled cartridge should be clear to slightly yellow.

Do not use the prefilled cartridge if the liquid is discolored or cloudy.

Call scPharmaceuticals at: 1-855-SCPHARMA (1-855-727-4276) or call your healthcare provider.

STEP 3 Load Prefilled Cartridge into the On-Body Infusor

3.1 Clean the tip (small end) of the prefilled cartridge with an alcohol wipe (see Figure I).

Do not continue with the process of opening the cartridge holder all the way or loading the prefilled cartridge until you are ready to begin the infusion.

3.2 Open the cartridge holder all the way to turn on the on-body Infusor. The on-body Infusor “beeps” and the indicator light will begin blinking blue (see Figure J).

Note: Complete steps 3.3 through 6.1 within 30 minutes of fully opening the cartridge holder or the Infusor will alarm and cannot restart.

3.3 Insert the prefilled cartridge into the cartridge holder with the tip pointed down (see Figure K).

Note: The prefilled cartridge should slide into the cartridge holder easily. If it does not slide in easily, check the prefilled cartridge to make sure the tip is pointed down and try again.

Do not press the blue start button until on-body Infusor is applied to skin and you are ready to begin the infusion.

3.4 Close the cartridge holder all the way until it is even with the rest of the on-body Infusor (see Figure L). You may hear a “click” sound when it is closed.

Note: If the indicator light blinks red and the on-body Infusor "beeps", the on-body Infusor has experienced an internal error. Do not use the on-body Infusor (see On-Body Infusor Alarm section).

Apply the On-Body Infusor

STEP 4 Select and Prepare Application Site

4.1 Select one site on the stomach on either side of the belly button (navel). The site should be a flat area below the rib cage and above the belt line (see Figure M).

Do not select a site where the skin is irritated or broken.

Do not apply lotions, oils or ointments to the adhesion area of the abdomen.

Do not select a site where belts, waistbands or other types of clothing may rub against, disturb, or dislodge the on-body Infusor.

Note: Rotate application site (side of the stomach) each time if told by your healthcare provider to repeat dose.

4.2 The site should be hairless or nearly hairless. If needed, remove excess hair by clipping or shaving the hair before applying the on-body Infusor (see Figure N).

4.3 Wipe the skin where the on-body Infusor will be applied with an alcohol wipe and allow area to dry (see Figure O).

STEP 5 Apply the On-Body Infusor

5.1 Pick up the on-body Infusor. Peel away the adhesive liner by grasping the white tab and pulling it away from the blue tab/adhesive backing (see Figure P).

Do not touch the sticky (adhesive) part of the on-body Infusor with your fingers or let it touch any objects or surfaces before the Infusor is placed on the skin.

5.2 Apply the on-body Infusor to the chosen skin site while standing or sitting up straight.

Position the on-body Infusor so that the cartridge window and the indicator light can be seen during the infusion (see Figure Q).

Do not bend over when applying the on-body Infusor.

5.3 Press the on-body Infusor firmly onto the skin and hold it for several seconds (see Figure R). Then rub your finger over the edges of the adhesive to get it to stick well.

Do not touch the blue start button until you are ready to start the infusion (see Step 6).

Do not remove and reapply on-body Infusor. The on-body Infusor adhesive might not work as well.

Start the Infusion

STEP 6 Start the Infusion

6.1 Firmly press and release the blue start button to begin the infusion (see Figure S).

The on-body Infusor will stick a very small needle just under the skin and begin delivering the medicine. The indicator light will start blinking green and the on-body Infusor "beeps", signifying that the infusion has begun.

Note: At the start of the infusion, you may also hear the on-body Infusor motor running for several seconds.

STEP 7 Allow Medicine to Deliver for 5 Hours

7.1 Relax during the delivery period. The on-body Infusor should remain on the skin until the delivery is complete.

Do not exercise or take part in activities that might result in the on-body Infusor falling off. Take care not to bump the on-body Infusor while wearing it. It takes about 5 hours for the on-body Infusor to deliver all of the medicine. During the infusion, the indicator light will continue to blink green periodically, signifying that the infusion is running (see Figure T).

Note: If the on-body Infusor falls off or if the indicator light begins blinking red, call your healthcare provider right away (see On-Body Infusor Alarm section). Do not reapply or reuse the on-body Infusor. Do not apply a new on-body Infusor unless instructed to do so by your healthcare provider.

If You Have to Stop the Infusion Due to An Emergency, Do the Following:

- Remove the on-body Infusor from the skin (see Step 8). It will immediately stop infusing and the on-body Infusor will deactivate. Do not reuse the on-body Infusor. After the on-body Infusor is removed, it can no longer be used.
- Call your healthcare provider for further instructions.

Remove and Dispose of the On-Body Infusor

STEP 8 When Infusion is Complete, Remove the On-Body Infusor from the Skin

8.1 The infusion is complete and the on-body Infusor is ready to be removed when (see Figure U):

- The indicator light turns solid green.
- The on-body Infusor "beeps".
- The white plunger rod fills the cartridge window all the way.

Note: If indicator light begins blinking red instead of green and the on-body Infusor “beeps”, call your healthcare provider (see On-Body Infusor Alarm section).

8.2 Peel the on-body Infusor off the skin by holding the skin down and pulling on the blue tab (see Figure V). When the on-body Infusor is removed, the indicator light will turn off, the needle cover will extend over the needle to protect against accidental needle sticks, and the on-body Infusor will turn off.

Note: You might have some discomfort after you remove the adhesive. This discomfort should quickly go away. However, some redness of the skin may remain.

8.3 Check the infusion site. If there is any bleeding use a cotton ball or apply a small adhesive bandage.

STEP 9 Throw Away (Dispose) of Used On-Body Infusor

9.1 Dispose of the used FUROSCIX On-Body Infusor and prefilled cartridge together into an FDA-cleared sharps container (see Figure W).

Do not attempt to remove the cartridge from the on-body Infusor; it cannot be removed.

Do not throw away the used on-body Infusor into household trash.

If you do not have a FDA-cleared sharps disposal container, you may use a household container that is:

- made of a heavy-duty plastic,
- can be closed with a tight-fitting, puncture-resistant lid, without sharps being able to come out,
- upright and stable during use,
- leak-resistant, and
- properly labeled to warn of hazardous waste inside the container.

When your sharps disposal container is almost full, you will need to follow your community guidelines for the right way to dispose of your sharps disposal container. There may be state or local laws about how you should throw away used Needles and syringes. For more information about safe sharps disposal, and for specific information about sharps disposal in the state that you live in, go to the FDA’s website at: http://www.fda.gov/safesharpsdisposal.

Do not dispose of your used sharps disposal container in your household trash unless your community guidelines permit this.

Do not recycle the on-body Infusor or sharps disposal container or throw them into household trash.

Important: Always keep the sharps disposal container out of the reach of children.

For more information refer to: http://www.safeneedledisposal.org

Infusor Alarm

What happened?

The Indicator light blinks red and the on-body Infusor "beeps" (see Figure X).

What does it mean?

There has been an internal error or the on-body Infusor came off the skin during the infusion.

What to do?

Stop using the on-body Infusor. If the on-body Infusor is on the skin, carefully remove it. Call your healthcare provider for further instructions.

Do not reapply or reuse the on-body Infusor. It can no longer be used.

Do not apply a new on-body Infusor unless instructed to do so by your healthcare provider.

Symbols Legend

scPharmaceuticals, Inc.

25 Mall Road, Suite 203, Burlington, MA 01803

1-855-SCPHARMA (1-855-727-4276)

This Instructions for Use has been approved by the U.S. Food and Drug Administration.

Issued: 10/2023

Reg-0017 Rev 01

PACKAGE LABEL

Cartridge Carton

NDC 71767-100

FUROSCIX®

(furosemide injection)

80 mg/10 mL

(8 mg/mL)

10 mL Single Dose Cartridge

FOR SUBCUTANEOUS USE ONLY

Rx Only

PACKAGE LABEL

Cartridge

NDC 71767-100

FUROSCIX®

(furosemide injection)

80 mg/10 mL

(8 mg/mL)

10 mL Single Dose Cartridge

FOR SUBCUTANEOUS USE ONLY

Rx Only

PACKAGE LABEL

Device Tyvek Lid

On-Body Infusor for

FUROSCIX®

(furosemide injection)
80 mg/10 mL (8 mg/mL)
For subcutaneous use

PACKAGE LABEL

Device (Direct Pad Printing)

On-Body Infusor for

FUROSCIX®

(furosemide injection)
80 mg/10 mL (8 mg/mL)
For subcutaneous use

PACKAGE LABEL

Combination Product Primary Carton

NDC 71767-100-01

1 X 10 mL Single Dose Prefilled Cartridge

1 X Single Use On-Body Infusor

FUROSCIX®

(furosemide injection)

80 mg/10 mL

(8 mg/mL)

FOR SUBCUTANEOUS USE ONLY

Single Dose

Rx Only

PACKAGE LABEL

Combination Product Physician Sample Primary Carton

NDC 71767-100-01

PHYSICIAN SAMPLE ONLY

NOT FOR SALE

1 X 10 mL Single Dose Prefilled Cartridge

1 X Single Use On-Body Infusor

FUROSCIX®

(furosemide injection)

80 mg/10 mL

(8 mg/mL)

FOR SUBCUTANEOUS USE ONLY

Single Dose

Rx Only